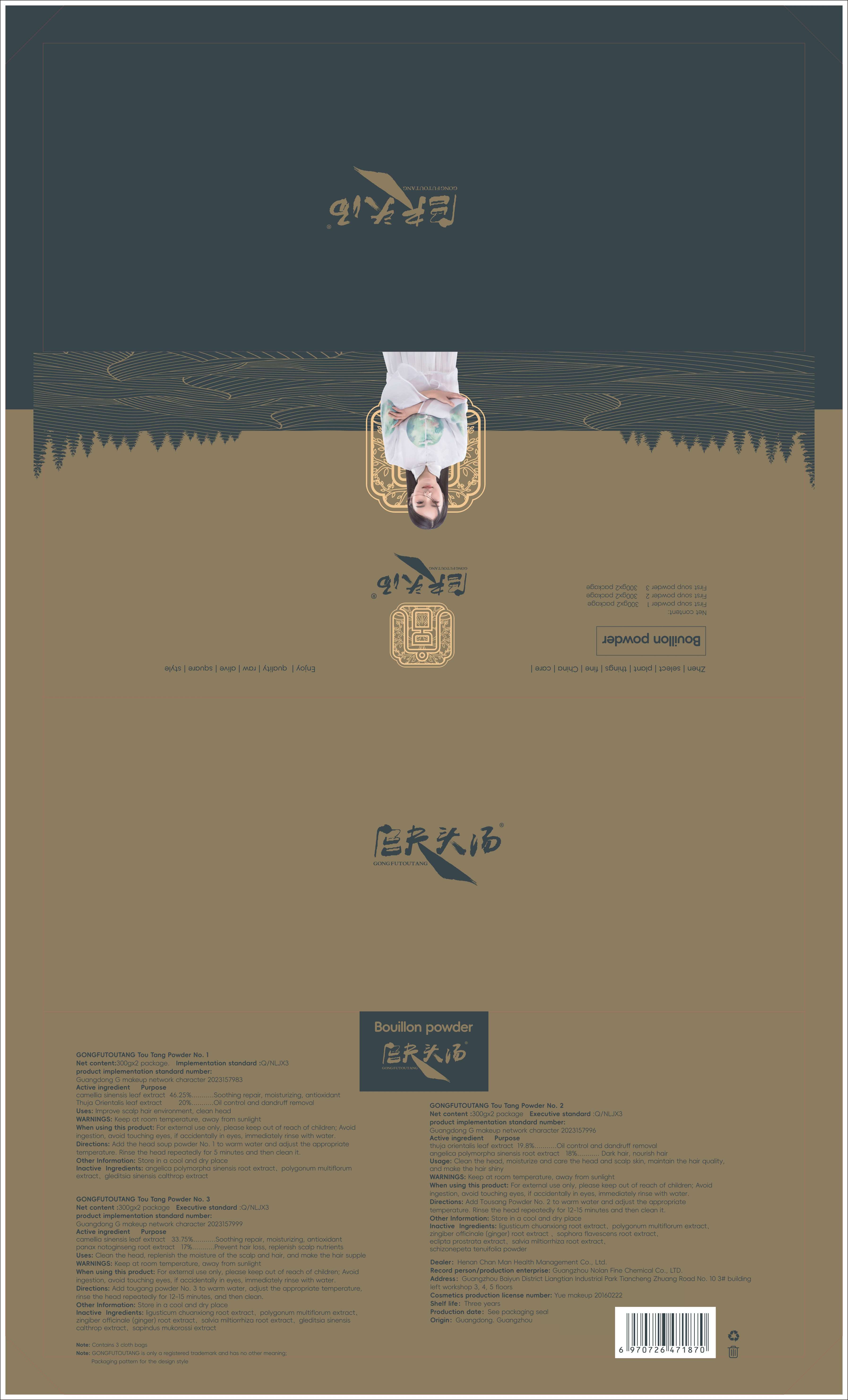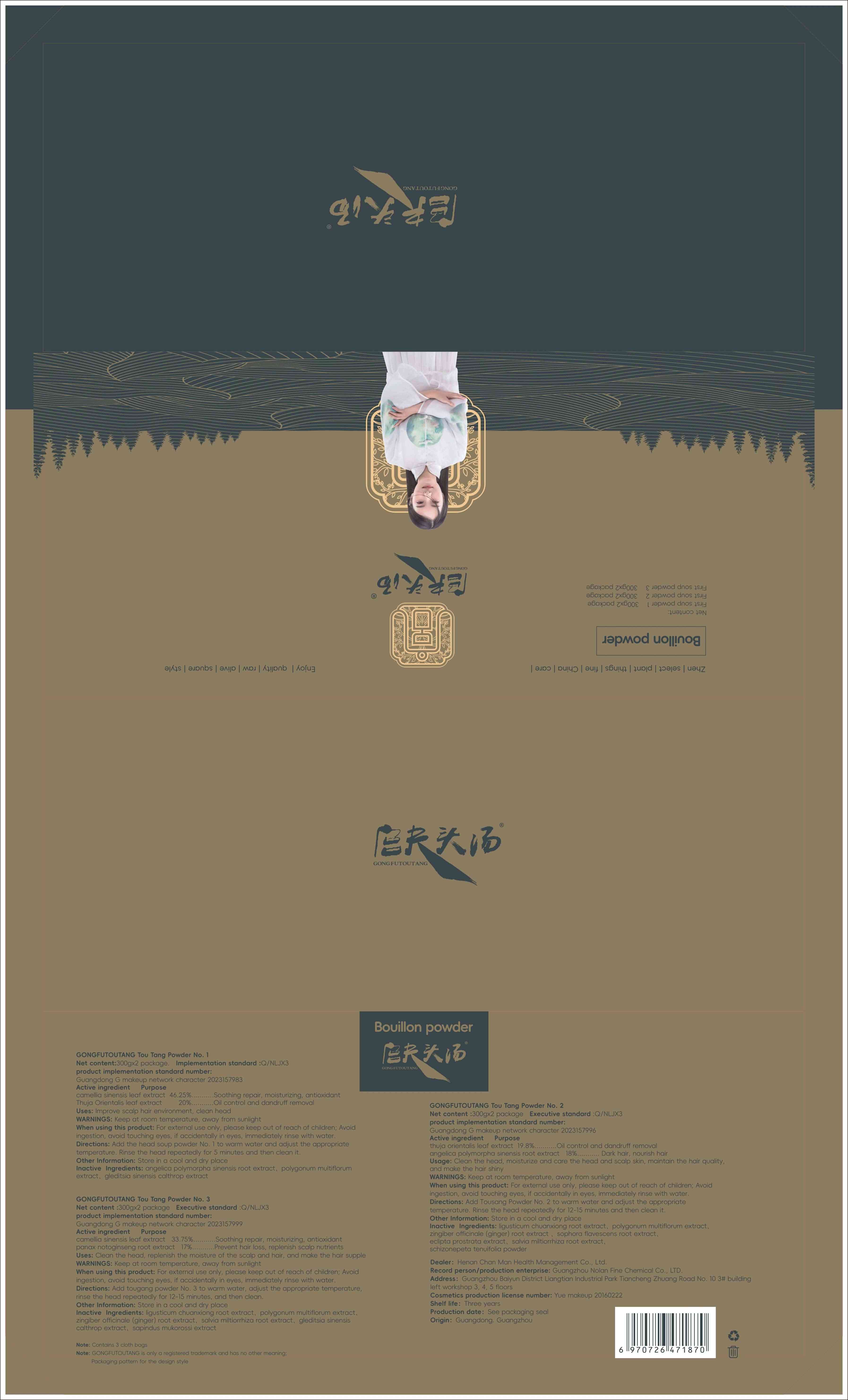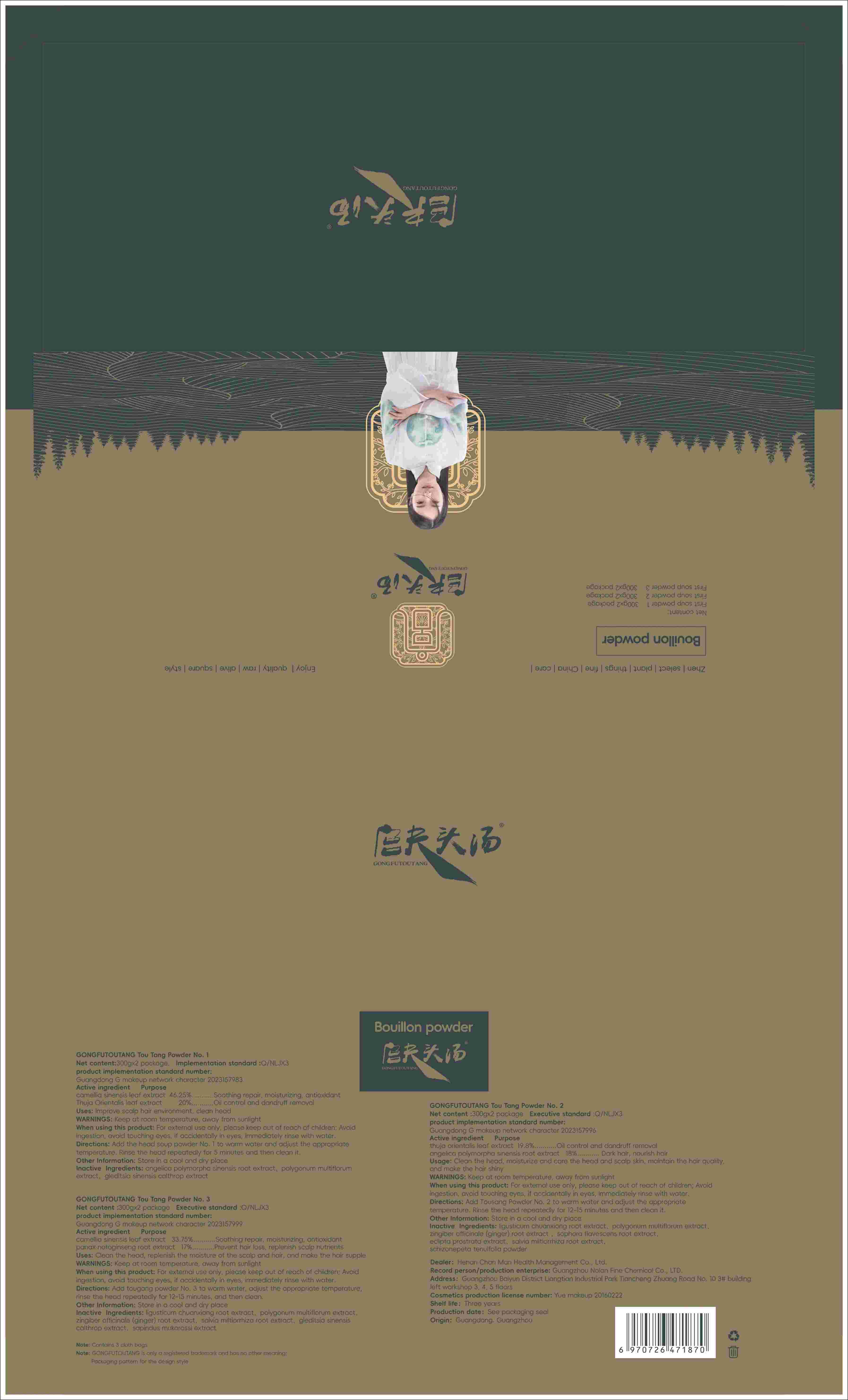 DRUG LABEL: GONGFUTOUTANG Tou Tang Powder No. 2
NDC: 84286-006 | Form: POWDER
Manufacturer: Henan Chanman Health Management Co., Ltd
Category: otc | Type: HUMAN OTC DRUG LABEL
Date: 20240507

ACTIVE INGREDIENTS: ANGELICA SINENSIS ROOT 18 g/100 g; PLATYCLADUS ORIENTALIS LEAF 19.8 g/100 g
INACTIVE INGREDIENTS: FALLOPIA MULTIFLORA ROOT; GINGER; SALVIA MILTIORRHIZA ROOT; SOPHORA FLAVESCENS ROOT; SCHIZONEPETA TENUFOLIA SPIKE; LIGUSTICUM SINENSE SUBSP. CHUANXIONG ROOT; ECLIPTA PROSTRATA LEAF

84286-005 006 007

Active Ingredient

GONGFUTOUTANG Tou Tang Powder No. 1

Camellia sinensis leaf extract 46.25%

Thuja Orientalis leaf extract 50%

GONGFUTOUTANG Tou Tang Powder No. 2

thuja orientalis leaf extract 19.8%

angelica polymorpha sinensis root extract 18%

GONGFUTOUTANG Tou Tang Powder No. 3

Camellia sinensis leaf extract 33.75%

panax notoginseng root extract 17%

Purpose

Soothing repair, moisturizing, antioxidant，Oil control and dandruff removal

Use

lmprove scalp hair environment, clean head

Warnings

Keep at room temperature, away from sunlight

When Using

For external use only, please keep out of reach of children; Avoidingestion, avoid touching eyes, if accidentally in eyes, immediately rinse with water.

Keep Oot Of Reach Of Children

keep out of reach of children

Directions

Add the head soup powder No. 1 to warm water and adjust the appropriatetemperature. Rinse the head repeatedly for 5 minutes and then clean it.

Other information

Store in a cool and dry place

Inactive ingredients

GONGFUTOUTANG Tou Tang Powder No. 1

angelica polymorpha sinensis root extract

polygonum multiflorum extract

gleditsia sinensis calthrop extract

GONGFUTOUTANG Tou Tang Powder No. 2

ligusticum chuanxiong root extract

polygonum multiflorum extract

zingiber officinale (ginger) root extract

sophora flavescens root extract

eclipta prostrata extract

salvia miltiorrhiza root extract

schizonepeta tenuifolia powder

GONGFUTOUTANG Tou Tang Powder No. 3

ligusticum chuanxiong root extract

polygonum multiflorum extract

zingiber officinale (ginger) root extract

salvia miltiorrhiza root extract

gleditsia sinensiscalthrop extract

sapindus mukorossi extract